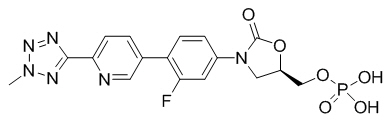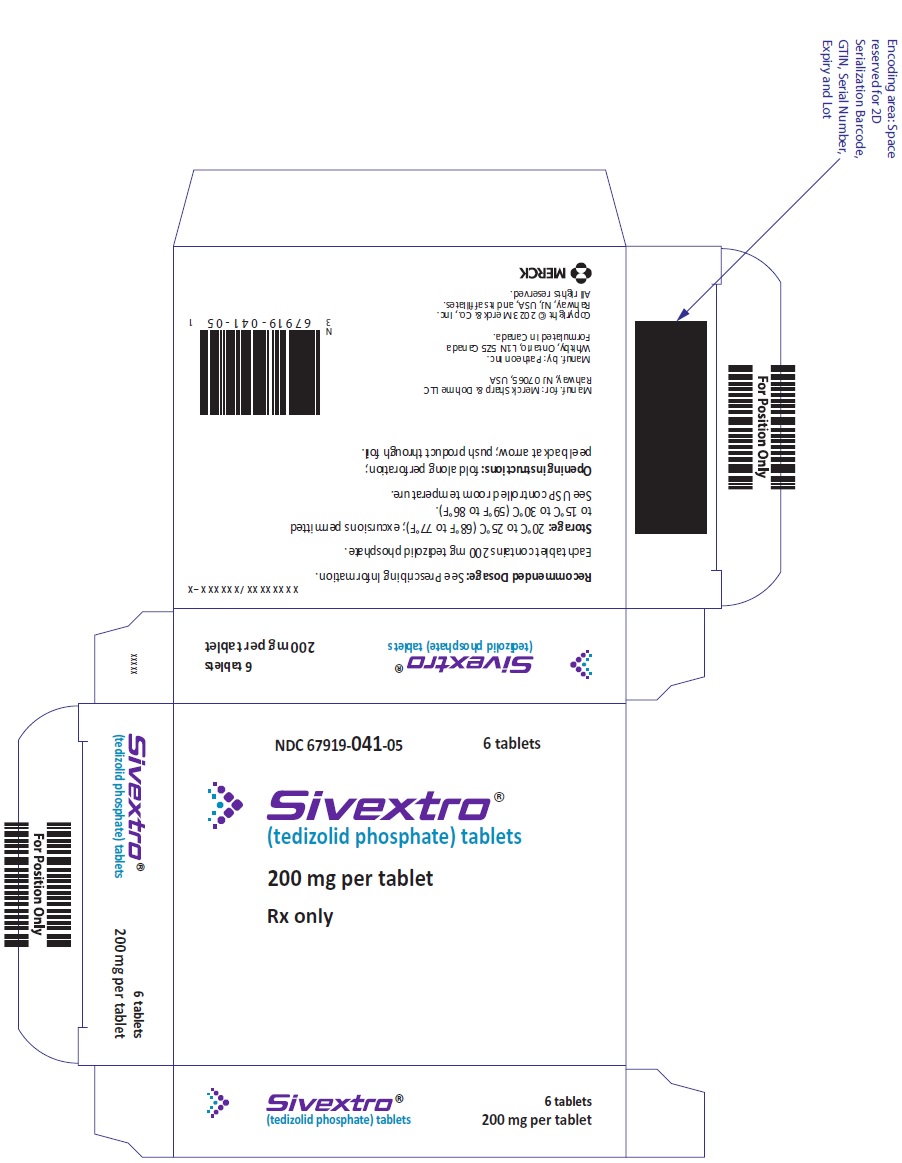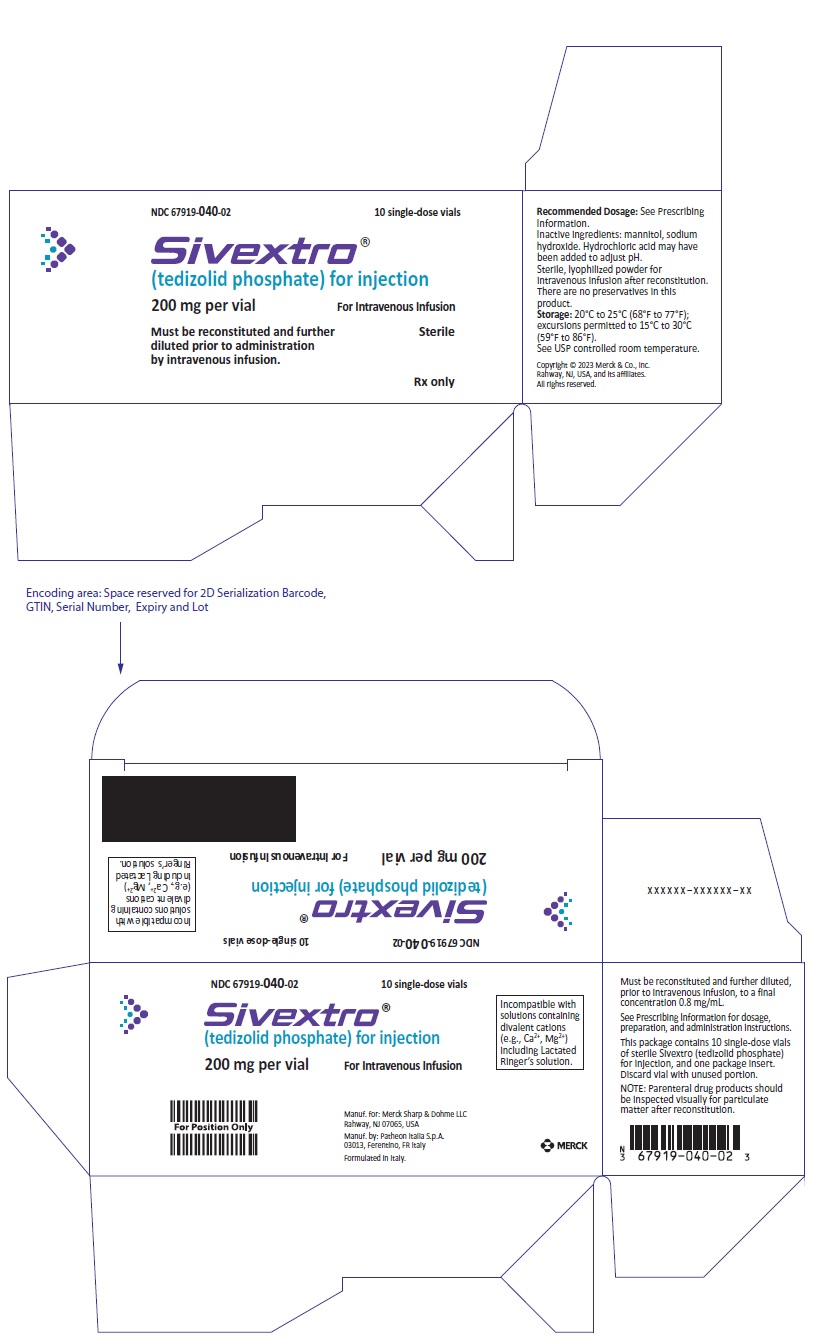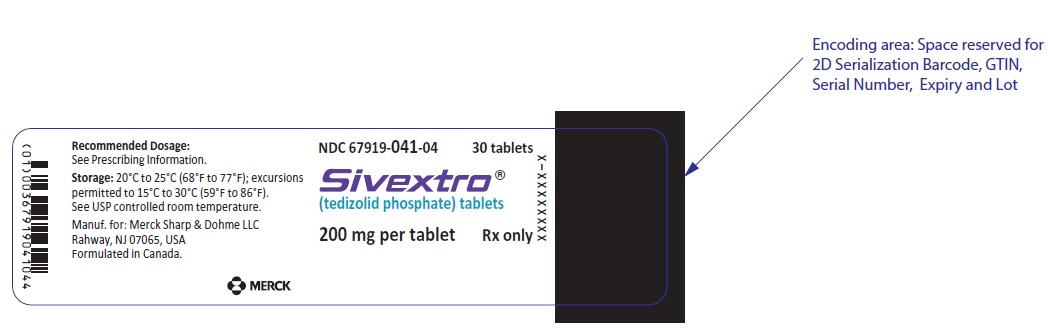 DRUG LABEL: SIVEXTRO
NDC: 67919-041 | Form: TABLET, FILM COATED
Manufacturer: Merck Sharp & Dohme LLC
Category: prescription | Type: HUMAN PRESCRIPTION DRUG LABEL
Date: 20250404

ACTIVE INGREDIENTS: tedizolid phosphate 200 mg/1 1
INACTIVE INGREDIENTS: MICROCRYSTALLINE CELLULOSE; mannitol; crospovidone (15 MPA.S AT 5%); POVIDONE, UNSPECIFIED; magnesium stearate; POLYVINYL ALCOHOL, UNSPECIFIED; titanium dioxide; POLYETHYLENE GLYCOL, UNSPECIFIED; talc; ferric oxide yellow

HIGHLIGHTS OF PRESCRIBING INFORMATION

These highlights do not include all the information needed to use SIVEXTRO® safely and effectively. See full prescribing information for SIVEXTRO.
SIVEXTRO (tedizolid phosphate) for injection, for intravenous use
SIVEXTRO (tedizolid phosphate) tablet, for oral use
Initial U.S. Approval: 2014

RECENT MAJOR CHANGES

Indications and Usage (1.1, 1.2) | 4/2025
Dosage and Administration (2.1, 2.2, 2.3, 2.4, 2.5, 2.6, 2.7) | 4/2025

1 INDICATIONS AND USAGE

SIVEXTRO is an oxazolidinone antibacterial indicated for the treatment of acute bacterial skin and skin structure infections (ABSSSI) caused by designated susceptible microorganisms in adult and pediatric patients (at least 26 weeks gestational age and weighing at least 1 kg) (1.1)

Usage to Reduce Development of Drug-Resistant Bacteria
To reduce the development of drug-resistant bacteria and maintain the effectiveness of SIVEXTRO and other antibacterial drugs, SIVEXTRO should be used only to treat or prevent infections that are proven or strongly suspected to be caused by susceptible bacteria.

2 DOSAGE AND ADMINISTRATION

- Do not administer SIVEXTRO Tablets to pediatric patients weighing less than 35 kg. (2.1)
- Adult Patients Intravenous and Oral Dosage: 200 mg administered once daily orally or as an intravenous (IV) infusion over 1 hour for 6 days as specified in Table 1 in the full prescribing information. (2.2)
- Pediatric Patients Intravenous Dosage (at least 26 weeks gestational age and weighing at least 1 kg): Weight-based dosing as an intravenous infusion as specified in Table 2 in the full prescribing information. (2.3)
- Pediatric Patients Oral Dosage (weighing greater than or equal to 35 kg): Weight-based dosing as an oral tablet administered once daily as specified in Table 3 in the full prescribing information. (2.3)

3 DOSAGE FORMS AND STRENGTHS

- For injection: 200 mg, sterile, lyophilized powder in single-dose vial for reconstitution for intravenous infusion. (3)
- Tablet: 200 mg (3)

4 CONTRAINDICATIONS

None (4)

5 WARNINGS AND PRECAUTIONS

- Patients with neutropenia: The safety and efficacy of SIVEXTRO in patients with neutropenia (neutrophil counts <1000 cells/mm^3) have not been adequately evaluated. In an animal model of infection, the antibacterial activity of SIVEXTRO was reduced in the absence of granulocytes. Consider alternative therapies in neutropenic patients. (5.1)
- Clostridioides difficile-associated diarrhea: Evaluate if diarrhea occurs. (5.2)

6 ADVERSE REACTIONS

- The most common adverse reactions (≥2%) in adult patients are nausea, headache, diarrhea, infusion- or injection-related adverse reactions, vomiting, and dizziness. (6.1)
- The most common adverse reactions (>2%) in pediatric patients (12 years to less than 18 years of age) are phlebitis and increased hepatic transaminases. (6.1)
- The most common adverse reactions (>2%) in pediatric patients (less than 12 years of age) are infusion- or injection-related adverse reactions and vomiting. (6.1)

To report SUSPECTED ADVERSE REACTIONS, contact Merck Sharp & Dohme LLC at 1-877-888-4231 or FDA at 1-800-FDA-1088 or www.fda.gov/medwatch .

7 DRUG INTERACTIONS

SIVEXTRO (when administered orally) can increase the plasma concentrations of orally administered Breast Cancer Resistance Protein (BCRP) substrates. Monitor for adverse reactions related to the concomitant BCRP substrates if coadministration cannot be avoided. (7, 12.3)

8 USE IN SPECIFIC POPULATIONS

Pregnancy: Based on animal data, SIVEXTRO may cause fetal harm. Advise pregnant women of the potential risks to a fetus. (8.1)

FULL PRESCRIBING INFORMATION

1 INDICATIONS AND USAGE

1.1 Acute Bacterial Skin and Skin Structure Infections

SIVEXTRO® is indicated for the treatment of acute bacterial skin and skin structure infections (ABSSSI) caused by susceptible isolates of the following gram-positive microorganisms: Staphylococcus aureus (including methicillin-resistant [MRSA] and methicillin-susceptible [MSSA] isolates), Streptococcus pyogenes, Streptococcus agalactiae, Streptococcus anginosus Group (including Streptococcus anginosus, Streptococcus intermedius, and Streptococcus constellatus), and Enterococcus faecalis, in adult and pediatric patients (at least 26 weeks gestational age and weighing at least 1 kg).

1.2 Usage to Reduce Development of Drug-Resistant Bacteria

To reduce the development of drug-resistant bacteria and maintain the effectiveness of SIVEXTRO and other antibacterial drugs, SIVEXTRO should be used only to treat infections that are proven or strongly suspected to be caused by susceptible bacteria. When culture and susceptibility information are available, they should be considered in selecting or modifying antibacterial therapy. In the absence of such data, local epidemiology and susceptibility patterns may contribute to the empiric selection of therapy.

2 DOSAGE AND ADMINISTRATION

2.1 Important Administration Instructions for Pediatric Patients Weighing Less than 35 kg

Do not administer SIVEXTRO Tablets to pediatric patients weighing less than 35 kg [see Dosage and Administration 2.3].

2.2 Recommended Dosage for Adult Patients

The recommended dosage of SIVEXTRO is 200 mg administered once daily for six (6) days either as an oral tablet (with or without food) or as an intravenous (IV) infusion in adult patients.

The recommended dosage and administration of SIVEXTRO in adult patients are described in Table 1.

Table 1: Recommended Dosage of SIVEXTRO for Adult Patients
Infection | Route | Dose | Frequency | Infusion Time | Duration of Treatment
Acute Bacterial Skin and Skin Structure Infections (ABSSSI) | Intravenous | 200 mg | Once daily | 1 hour | 6 days
Acute Bacterial Skin and Skin Structure Infections (ABSSSI) | Oral | 200 mg | Once daily | Not Applicable | 6 days

No dose adjustment is necessary when changing from intravenous to oral SIVEXTRO.

2.3 Recommended Dosage for Pediatric Patients

Recommended Dosage of SIVEXTRO for Injection for Pediatric Patients: Intravenous Dosage

The recommended intravenous dosage of SIVEXTRO for Injection for pediatric patients (at least 26 weeks gestational age and weighing at least 1 kg) is presented in Table 2.

Table 2: Recommended Intravenous Dosage of SIVEXTRO for Injection for Pediatric Patients
Weight Band (kg) | Dose | Frequency | Infusion Time | Duration of Treatment
Pediatric Patients Weighing Less than 2 kg
1 to less than 2 [Recommended Dosage for 1 kg to less than 2 kg is based on actual body weight.] | 3 mg/kg | Twice daily | 1 hour | 6 days
Pediatric Patients Weighing at Least 2 kg
2 to less than 3 | 6 mg | Twice daily | 1 hour | 6 days
3 to less than 6 | 12 mg | Twice daily | 1 hour | 6 days
6 to less than 10 | 20 mg | Twice daily | 1 hour | 6 days
10 to less than 14 | 30 mg | Twice daily | 1 hour | 6 days
14 to less than 20 | 40 mg | Twice daily | 1 hour | 6 days
20 to less than 35 | 60 mg | Twice daily | 1 hour | 6 days
Pediatric Patients Weighing at Least 35 kg
Greater than or equal to 35 | 200 mg | Once daily | 1 hour | 6 days

Recommended Dosage of SIVEXTRO Tablets for Pediatric Patients: Oral Dosage

The recommended oral dosage of SIVEXTRO Tablets for pediatric patients is presented in Table 3. SIVEXTRO Tablets can be administered with or without food. Do not administer SIVEXTRO Tablets to pediatric patients weighing less than 35 kg.

Table 3: Recommended Oral Tablet Dosage of SIVEXTRO for Pediatric Patients
Weight Band (kg) | Dose | Frequency | Duration of Treatment
Greater than or equal to 35 | 200 mg | Once daily | 6 days

No dose adjustment is necessary when changing from intravenous to oral SIVEXTRO.

2.4 Recommendations Regarding Missed Doses(s)

For Once Daily Oral Dosing of SIVEXTRO Tablets

If patients miss a dose, administer the dose as soon as possible anytime up to 8 hours prior to their next scheduled dose. If less than 8 hours remain before the next dose, instruct the patients to wait until their next scheduled dose.

2.5 Preparation and Administration of Intravenous Solution

SIVEXTRO is supplied as a sterile, lyophilized powder for injection in single-dose vials of 200 mg. Each 200 mg vial must be reconstituted with Sterile Water for Injection and subsequently diluted with 0.9% Sodium Chloride Injection, USP or 5% Dextrose Injection, USP.

SIVEXTRO vials contain no antimicrobial preservatives and are intended for single dose only. Discard any unused portion.

Preparation of SIVEXTRO for Injection

Parenteral drug products should be inspected visually for particulate matter and discoloration prior to administration, whenever solution and container permit.

The contents of the vial should be reconstituted using aseptic technique as follows:

Note: To minimize foaming, AVOID vigorous agitation or shaking of the vial during or after reconstitution.

For Adults and Pediatric Patients Weighing at Least 35 kg:

1. Reconstitute the SIVEXTRO vial with 4 mL of Sterile Water for Injection to provide a concentration of 50 mg/mL in each vial.
2. Gently swirl the contents and let the vial stand until the cake has completely dissolved and any foam disperses.
  Inspect the vial to ensure the solution contains no particulate matter and no cake or powder remains attached to the sides of the vial. If necessary, invert the vial to dissolve any remaining powder and swirl gently to prevent foaming. The reconstituted solution is clear and colorless to pale-yellow in color; the total time from reconstitution to the end of administration should not exceed 24 hours at either room temperature or under refrigeration at 2°C to 8°C (36°F to 46°F).
  Tilt the upright vial and insert a syringe with appropriately sized needle into the bottom corner of the vial and remove 4 mL of the reconstituted solution for the 200 mg dose. Do not invert the vial during extraction.
3. The reconstituted solution must be further diluted in 250 mL of 0.9% Sodium Chloride Injection, USP or 5% Dextrose Injection, USP. Slowly inject the required volume of reconstituted solution as determined in Step 2 into a 250 mL bag of 0.9% Sodium Chloride Injection, USP or 5% Dextrose Injection, USP. Invert the bag gently to mix. Do NOT shake the bag as this may cause foaming.

For Pediatric Patients Weighing Less than 35 kg:

1. Reconstitute the SIVEXTRO vial with 4 mL of Sterile Water for Injection to provide a concentration of 50 mg/mL in each vial.
2. Gently swirl the contents and let the vial stand until the cake has completely dissolved and any foam disperses.
3. Inspect the vial to ensure the solution contains no particulate matter and no cake or powder remains attached to the sides of the vial. If necessary, invert the vial to dissolve any remaining powder and swirl gently to prevent foaming. The reconstituted solution is clear and colorless to pale-yellow in color; the total time from reconstitution to the end of administration should not exceed 24 hours at either room temperature or under refrigeration at 2°C to 8°C (36°F to 46°F).
  Prepare a stock solution (100 mL of 0.8 mg/mL tedizolid phosphate): Tilt the upright vial and insert a syringe with appropriately sized needle into the bottom corner of the vial and remove 1.6 mL of the reconstituted solution and add it to an infusion bag containing 98.4 mL of 0.9% Sodium Chloride Injection, USP or 5% Dextrose Injection, USP. Do not invert the vial during extraction.
4. Prepare the required volume of stock solution for infusion: Refer to Table 4 to convert the dose in mg to the appropriate volume of stock solution to be administered. Transfer this volume of stock solution to an adequately sized infusion bag or infusion syringe. It may be necessary to round to the nearest graduation mark of an appropriately sized syringe for smaller volumes. The total time from reconstitution to the end of administration should not exceed 24 hours at either room temperature or under refrigeration at 2°C to 8°C (36°F to 46°F).

Table 4: Preparation of SIVEXTRO for Injection for Pediatric Patients Weighing 1 kg to Less than 35 kg from the 100 mL Stock Solution of 0.8 mg/mL Tedizolid Phosphate
Body Weight (kg) | Amount of SIVEXTRO per dose (given twice daily) | Volume of stock solution (0.8 mg/mL) to be transferred to an adequately sized infusion bag or infusion syringe
Pediatric Patients Weighing Less than 2 kg
1 to less than 2 | 3 mg/kg | Volume (mL) = Weight (kg) x 3.75 mL/kg
Pediatric Patients Weighing at Least 2 kg
2 to less than 3 | 6 mg | 7.5 mL
3 to less than 6 | 12 mg | 15 mL
6 to less than 10 | 20 mg | 25 mL
10 to less than 14 | 30 mg | 37.5 mL
14 to less than 20 | 40 mg | 50 mL
20 to less than 35 | 60 mg | 75 mL

Administration of SIVEXTRO for Injection

Administer SIVEXTRO for Injection as an intravenous infusion only.

Do not administer as an intravenous push or bolus. Do not mix SIVEXTRO for Injection with other drugs when administering. It is not intended for intra-arterial, intramuscular, intrathecal, intraperitoneal, or subcutaneous administration.

The intravenous bag containing the reconstituted and diluted intravenous solution should be inspected visually for particulate matter prior to administration. Discard if visible particles are observed. The resulting solution is clear and colorless to pale-yellow in color.

After reconstitution and dilution, SIVEXTRO for Injection is to be administered via intravenous infusion using a total time of 1 hour.

The total time from reconstitution to the end of administration of SIVEXTRO for Injection should not exceed 24 hours at either room temperature or under refrigeration at 2°C to 8°C (36°F to 46°F).

Discard unused portion.

2.6 Compatible Intravenous Solutions

SIVEXTRO is compatible with 0.9% Sodium Chloride Injection, USP and 5% Dextrose Injection, USP.

Limited data are available on the compatibility of SIVEXTRO for Injection with other intravenous substances, additives or other medications and they should not be added to SIVEXTRO single-dose vials or infused simultaneously. If the same intravenous line is used for sequential infusion of several different drugs, the line should be flushed before and after infusion of SIVEXTRO with 0.9% Sodium Chloride Injection, USP.

2.7 Incompatibilities

SIVEXTRO for Injection is incompatible with any solution containing divalent cations (e.g., Ca^2+, Mg^2+), including Lactated Ringer’s Injection and Hartmann’s Solution.

3 DOSAGE FORMS AND STRENGTHS

SIVEXTRO 200 mg tablet is a yellow film-coated oval tablet; each tablet is debossed with "TZD" on one side and "200" on the other side.

SIVEXTRO for Injection is a sterile, white to off-white lyophilized powder for injection in single-dose vials of 200 mg. Each 200 mg vial must be reconstituted with Sterile Water for Injection and subsequently diluted with 0.9% Sodium Chloride Injection, USP or 5% Dextrose Injection, USP.

4 CONTRAINDICATIONS

None.

5 WARNINGS AND PRECAUTIONS

5.1 Patients with Neutropenia

The safety and efficacy of SIVEXTRO in patients with neutropenia (neutrophil counts <1000 cells/mm^3) have not been adequately evaluated. In an animal model of infection, the antibacterial activity of SIVEXTRO was reduced in the absence of granulocytes [see Clinical Pharmacology (12.2)]. Alternative therapies should be considered when treating patients with neutropenia and ABSSSI.

5.2 Clostridioides difficile-Associated Diarrhea

Clostridioides difficile-associated diarrhea (CDAD) has been reported for nearly all systemic antibacterial agents including SIVEXTRO, with severity ranging from mild diarrhea to fatal colitis. Treatment with antibacterial agents can alter the normal flora of the colon and may permit overgrowth of C. difficile.

C. difficile produces toxins A and B which contribute to the development of CDAD. Hypertoxin producing strains of C. difficile cause increased morbidity and mortality, as these infections can be refractory to antibacterial therapy and may require colectomy. CDAD must be considered in all patients who present with diarrhea following antibacterial drug use. Careful medical history is necessary because CDAD has been reported to occur more than two months after the administration of antibacterial agents.

If CDAD is suspected or confirmed, antibacterial use not directed against C. difficile should be discontinued, if possible. Appropriate measures such as fluid and electrolyte management, protein supplementation, antibacterial treatment of C. difficile, and surgical evaluation should be instituted as clinically indicated.

5.3 Development of Drug-Resistant Bacteria

Prescribing SIVEXTRO in the absence of a proven or strongly suspected bacterial infection or prophylactic indication is unlikely to provide benefit to the patient and increases the risk of the development of drug-resistant bacteria.

6 ADVERSE REACTIONS

6.1 Clinical Trials Experience

Because clinical trials are conducted under widely varying conditions, adverse reaction rates observed in clinical trials of a drug cannot be compared directly to rates from clinical trials of another drug and may not reflect rates observed in practice.

Clinical Trials Experience in Adult Patients

Adverse reactions were evaluated for 1425 adult patients treated with SIVEXTRO in two Phase 2 and four Phase 3 clinical trials (three Phase 3 trials for 6 days of therapy and one Phase 3 trial for 7-21 days of therapy). The median age of adult patients treated with SIVEXTRO in the Phase 2 and Phase 3 trials was 44 years, ranging between 17 and 94 years old. The majority of adult patients treated with SIVEXTRO were male (66%) and White (67%).

Serious Adverse Reactions and Adverse Reactions Leading to Discontinuation in Adults

Serious adverse reactions occurred in 37/1425 (2.6%) of adult patients treated with SIVEXTRO and in 25/1000 (2.5%) of adult patients treated with the comparator. SIVEXTRO was discontinued due to an adverse reaction in 14/1425 (1%) of adult patients and the comparator was discontinued due to an adverse reaction in 13/1000 (1.3%) of adult patients.

Most Common Adverse Reactions in Adults

The most common adverse reactions in adult patients treated with SIVEXTRO were nausea (7.1%), headache (4.5%), diarrhea (3.6%), vomiting (2.7%), and dizziness (1.6%). The median time of onset of adverse reactions was 5 days for both SIVEXTRO and linezolid with 12% occurring on the second day of treatment in both treatment groups.

Table 5 lists selected adverse reactions occurring in at least 2% of adult patients treated with SIVEXTRO in clinical trials.

Table 5: Selected Adverse Reactions Occurring in ≥2% of Adult Patients Receiving SIVEXTRO in the Pooled Phase 3 ABSSSI Clinical Trials
Adverse Reactions | Pooled Phase 3 ABSSSI Clinical Trials
Adverse Reactions | SIVEXTRO (200 mg oral/intravenous once daily for 6 days) (N=1037) | Linezolid (600 mg oral/intravenous twice daily for 10 days) (N=1000)
Gastrointestinal Disorders
Nausea | 7% | 10%
Diarrhea | 4% | 5%
Vomiting | 3% | 5%
Nervous System Disorder
Headache | 5% | 5%
Dizziness | 2% | 2%
Infusion- or Injection-Related Adverse Reactions [Includes adverse reactions in the following body system or organ classes: General disorders and administration site conditions, infections and infestations, injury, poisoning and procedural complications, and vascular disorders, including but not limited to, phlebitis, injection- or infusion-site pain, injection- or infusion-site swelling, injection-site reaction, injection-site erythema, injection-site induration, and infusion-related reaction.]
 | 4% | 2%

The following selected adverse reactions were reported in SIVEXTRO-treated adult patients at a rate of less than 2% in these clinical trials:

Blood and Lymphatic System Disorders: anemia

Cardiovascular: palpitations, tachycardia

Eye Disorders: asthenopia, vision blurred, visual impairment, vitreous floaters

Immune System Disorders: drug hypersensitivity

Infections and Infestations: Clostridioides difficile colitis, oral candidiasis, vulvovaginal mycotic infection

Investigations: hepatic transaminases increased (ALT increased, AST increased), gamma-glutamyltransferase (GGT) increased, white blood cell count decreased

Nervous System Disorders: hypoesthesia, paresthesia, VIIth nerve paralysis

Psychiatric Disorders: insomnia

Skin and Subcutaneous Tissue Disorders: pruritus, urticaria, dermatitis

Vascular Disorders: flushing, hypertension

Laboratory Parameters

Hematology laboratory abnormalities that were determined to be potentially clinically significant in the pooled Phase 3 ABSSSI clinical trials are provided in Table 6.

Table 6: Potentially Clinically Significant Lowest Laboratory Values in the Pooled Phase 3 ABSSSI Clinical Trials in Adults
Laboratory Assay | Potentially Clinically Significant Values [<75% (<50% for absolute neutrophil count) of lower limit of normal (LLN) for post-baseline measurements] , [Represents laboratory values within two days after the last dose of active drug]
Laboratory Assay | SIVEXTRO (200 mg oral/intravenous once daily for 6 days) (N) [Number of subjects with at least one post-baseline test result that are within two days after the last dose of active drug] | Linezolid (600 mg oral/intravenous twice daily for 10 days) (N)
Hemoglobin (<10.1 g/dL [M]) (<9 g/dL [F]) | (994) 3.4% | (957) 3.4%
Platelet count (<112 × 10^3/mm^3) | (989) 2.1% | (950) 3.8%
Absolute neutrophil count (<0.8 × 10^3/mm^3) | (980) 0.4% | (941) 0.6%
M = male; F = female

Myelosuppression

Phase 1 studies conducted in healthy adults exposed to SIVEXTRO for 21 days showed a possible dose and duration effect on hematologic parameters beyond 6 days of treatment. In the Phase 3 trials, clinically significant changes in these parameters were generally similar for both treatment arms (see Table 6). In postmarketing experience, thrombocytopenia has been reported in patients treated with SIVEXTRO. In one postmarketing report, patients who experienced thrombocytopenia were treated with tedizolid for a median duration of 26.5 days. A duration of treatment beyond 6 days is not approved.

Peripheral and Optic Neuropathy

Peripheral and optic neuropathy have been described in patients treated with another member of the oxazolidinone class for longer than 28 days. In Phase 3 trials in adults, reported adverse reactions for peripheral neuropathy and optic nerve disorders were similar between both treatment arms (peripheral neuropathy 1.2% vs. 0.7% for tedizolid phosphate and linezolid, respectively; optic nerve disorders 0.3% vs. 0.1%, respectively).

Clinical Trials Experience in Pediatric Patients

SIVEXTRO was evaluated in 166 pediatric patients with ABSSSI in two randomized, active-controlled clinical trials, including one in patients aged 12 years to less than 18 years and one in patients aged 4 months to less than 12 years (Pediatric Trial 1 and Pediatric Trial 2, respectively). Additionally, SIVEXTRO was evaluated in 47 pediatric patients less than 2 years of age with a suspected or confirmed gram-positive bacterial infection in an open-label clinical trial (pediatric Trial 3).

Pediatric Trial 1

Adverse Reactions

Pediatric Trial 1 was a randomized, active-controlled, single-blind clinical trial that enrolled pediatric patients aged 12 to less than 18 years with ABSSSI. A total of 91 pediatric patients were treated with IV and/or oral SIVEXTRO 200 mg for 6 days and 29 patients were treated with a comparator agent for 10 days. The majority of pediatric patients treated with SIVEXTRO were male (64%) and white (88%).

Serious adverse reactions occurred in 1/91 (1%) of pediatric patients treated with SIVEXTRO and in none of the 29 patients treated with the comparator. Adverse reactions leading to discontinuation occurred in 1 (1%) pediatric patient in the SIVEXTRO arm and in none in the comparator arm.

The most common adverse reactions occurring in those receiving SIVEXTRO in Pediatric Trial 1 were phlebitis (3%), increased hepatic transaminases (alanine aminotransferase, aspartate aminotransferase) (3%), anemia (1%), and vomiting (1%).

Laboratory Parameters

Table 7: Potentially Clinically Significant Lowest Laboratory Values in the ABSSSI Clinical Trial in Pediatric Patients (12 to <18 years)
Laboratory Assay | Potentially Clinically Significant Values [<75% (<50% for absolute neutrophil count) of lower limit of normal (LLN) for post-baseline measurements] , [Represents laboratory values within two days after the last dose of active drug]
Laboratory Assay | SIVEXTRO (200 mg oral/intravenous once daily for 6 days) (N) [Number of subjects with at least one post-baseline test result that are within two days after the last dose of active drug] | Comparators [5 IV and 4 oral comparators selected per local standard of care] (for 10 days) (N)
Hemoglobin (<10.1 g/dL [M]) (<9 g/dL [F]) | (85) 2.4% | (26) 0.0%
Platelet count (<112 × 10^3/mm^3) | (82) 1.2% | (26) 0.0%
Absolute neutrophil count (<0.8 × 10^3/mm^3) | (85) 0.0% | (26) 0.0%
M = male; F = female

Pediatric Trial 2

Pediatric Trial 2 was a randomized, active-controlled, single-blind clinical trial that enrolled pediatric patients aged 4 months to less than 12 years with ABSSSI. A total of 75 patients were treated with IV and/or oral SIVEXTRO for 6 to 10 days and 25 were treated with a comparator agent for 10 to 14 days. The oral suspension formulation (currently not an approved formulation) was used in the clinical trial for those receiving oral therapy [see Clinical Studies (14.1)]. The majority of patients treated with SIVEXTRO were male (53%) and white (77%), with a median age of 7 years and range of 0.3 to 11 years. The most common adverse reactions occurring in >2% of patients receiving SIVEXTRO in Pediatric Trial 2 were infusion- or injection-related adverse reactions (including catheter site pain, catheter occlusion, infusion site extravasation, phlebitis; 5%), and vomiting (4%).

Potentially clinically significant laboratory abnormalities in Pediatric Trial 2 included one patient treated with SIVEXTRO who developed thrombocytopenia with platelet count less than 100 × 10^3/mm^3.

Pediatric Trial 3

Pediatric Trial 3 was an open-label, pharmacokinetic and safety trial enrolling 47 pediatric patients less than 2 years of age as follows: ages 28 days to less than 2 years (N=14), term neonates from birth to less than 28 days (N=16), and pre-term neonates (gestational age ≥ 26 weeks) from birth to less than 28 days (N=17). In this single-arm trial, 39 patients aged less than 2 years with a suspected or confirmed gram-positive bacterial infection received a single-dose of IV or oral SIVEXTRO and 8 patients aged less than 28 days with a suspected or confirmed gram-positive bacterial infection received multiple doses of IV SIVEXTRO for 3 days. The majority of patients were male (62%) and white (55%), with a median age of 16 days (range 1 day to 608 days).

The safety profile observed in this pediatric population was similar to that observed in Pediatric Trials 1 and 2.

6.2 Postmarketing Experience

The following adverse reactions have been identified during post approval use of SIVEXTRO. Because these reactions are reported voluntarily from a population of uncertain size, it is not always possible to reliably estimate their frequency or establish a causal relationship to drug exposure.

Blood and Lymphatic System Disorders: thrombocytopenia

7 DRUG INTERACTIONS

Orally administered SIVEXTRO inhibits Breast Cancer Resistance Protein (BCRP) in the intestine, which can increase the plasma concentrations of orally administered BCRP substrates, and the potential for adverse reactions. If possible, an interruption in the treatment of the co-administered BCRP substrate medicinal product should be considered during treatment with SIVEXTRO, especially for BCRP substrates with a narrow therapeutic index (e.g., methotrexate or topotecan). If coadministration cannot be avoided, monitor for adverse reactions related to the concomitantly administered BCRP substrates, including rosuvastatin. [see Clinical Pharmacology (12.3).]

8 USE IN SPECIFIC POPULATIONS

8.1 Pregnancy

Risk Summary

Based on animal reproduction studies, SIVEXTRO may cause fetal harm when administered to pregnant women. The available data on the use of SIVEXTRO in pregnant women are insufficient to evaluate for a drug-associated risk of major birth defects, miscarriage, or adverse maternal or fetal outcomes. Advise pregnant women of the potential risks to a fetus. Fetal developmental toxicities were observed in mice and rats treated with SIVEXTRO. In embryo-fetal studies in mice and rats, tedizolid phosphate was shown to produce fetal developmental toxicities in mice and maternal toxicity and fetal developmental toxicities in rats. Tedizolid phosphate administered orally during organogenesis to pregnant animals was associated with reduced fetal weights and an increased incidence of costal cartilage anomalies in the absence of maternal toxicity in mice; and maternal toxicity, decreased fetal weights, and increased skeletal variations in rats at plasma exposures approximately 4 and 6 times respectively, the human plasma exposure at the maximum recommended human dose (MRHD) of 200 mg/day. In female rats administered tedizolid phosphate during organogenesis through lactation, there was no evidence of fetal toxicity, developmental delays, or impaired reproduction in the offspring at plasma exposures approximately equivalent to the human plasma exposure at the MRHD. (see Data)

The estimated background risk of major birth defects and miscarriage for the indicated population is unknown. All pregnancies have a background risk of birth defect, loss, or other adverse outcomes. In the U.S. general population, the estimated background risk of major birth defects and miscarriage in clinically recognized pregnancies is 2-4% and 15-20%, respectively.

Data

Animal Data

In an embryo-fetal development study, tedizolid phosphate administered orally to pregnant mice at doses of 1, 5, and 25 mg/kg/day during organogenesis (Gestational Day [GD] 6 to GD15) was associated with fetal developmental effects occurring in the absence of maternal toxicity, including reduced fetal weights and an increased incidence of costal cartilage anomalies at the high dose (approximately 4-times the human plasma exposure at the MRHD based on plasma AUC comparison). Tedizolid phosphate administered orally at doses of 2.5, 5, and 15 mg/kg/day to pregnant rats during organogenesis (GD6 through GD17) was associated with maternal toxicity (reduced maternal body weights), decreased fetal weights, and increased skeletal variations including reduced ossification of the sternebrae, vertebrae, and skull at the high dose of 15 mg/kg/day (approximately 6-times the human plasma exposure at the MRHD based on plasma AUC comparison). The doses not associated with fetal toxicity in mice and maternal and fetal toxicity in rats were 5 and 2.5 mg/kg/day respectively (for both species approximately equivalent to the human plasma exposure at the MRHD based on plasma AUC comparison).

In a pre-postnatal study, oral tedizolid phosphate administered to female rats at doses of 1.25, 2.5, and 3.75 mg/kg/day during gestation and lactation (GD6 through Lactational Day 20) was not associated with maternal toxicity, fetal toxicity, developmental delays, or impaired reproduction at doses up to the high dose of 3.75 mg/kg/day (approximately equivalent to the human plasma exposure at the MRHD based on plasma AUC comparison).

8.2 Lactation

Risk Summary

There is no information on the presence of tedizolid in human milk. Tedizolid is present in rat milk. When a drug is present in animal milk, it is likely that the drug will be present in human milk. There are no data on the effects of SIVEXTRO on the breastfed child or on milk production.

The developmental and health benefits of breastfeeding should be considered along with the mother's clinical need for SIVEXTRO and any potential adverse effects on the breastfed child from SIVEXTRO or from the underlying maternal condition.

8.4 Pediatric Use

The safety and effectiveness of SIVEXTRO for the treatment of ABSSSI have been established in pediatric patients at least 26 weeks gestational age and weighing at least 1 kg. Use of SIVEXTRO for the treatment of ABSSSI is supported by evidence from adequate and well-controlled studies in adults with additional pharmacokinetic and safety data in pediatric patients from birth (includes neonates at least 26 weeks gestational age) to less than 18 years of age [see Adverse Reactions (6.1), Clinical Pharmacology (12.3), and Clinical Studies (14.1)].

The safety and effectiveness of SIVEXTRO in pediatric patients less than 26 weeks gestational age and weighing less than 1 kg have not been established.

8.5 Geriatric Use

Clinical studies of SIVEXTRO did not include sufficient numbers of subjects aged 65 and over to determine whether they respond differently from younger subjects. No overall differences in pharmacokinetics were observed between elderly subjects and younger subjects.

10 OVERDOSAGE

In the event of overdosage, SIVEXTRO should be discontinued and general supportive treatment given. Hemodialysis does not result in meaningful removal of tedizolid from systemic circulation.

11 DESCRIPTION

SIVEXTRO (tedizolid phosphate), a phosphate prodrug, is converted to tedizolid in the presence of phosphatases.

Tedizolid phosphate has the chemical name [(5R)-(3-{3-Fluoro-4-[6-(2-methyl-2H-tetrazol- 5-yl) pyridin-3-yl]phenyl}-2-oxooxazolidin- 5-yl]methyl hydrogen phosphate.

Its empirical formula is C17H16FN6O6P and its molecular weight is 450.32. Its structural formula is:

Tedizolid phosphate is a white to yellow solid and is administered orally or by intravenous infusion.

The pharmacologically active moiety, tedizolid, is an antibacterial agent of the oxazolidinone class.

SIVEXTRO Tablets contain 200 mg of tedizolid phosphate, and the following inactive ingredients: crospovidone, magnesium stearate, mannitol, microcrystalline cellulose, and povidone. In addition, the film coating contains the following inactive ingredients: polyethylene glycol/macrogol, polyvinyl alcohol, talc, titanium dioxide, and yellow iron oxide.

SIVEXTRO for Injection is a sterile, white to off-white sterile lyophilized powder supplied in a clear glass single-dose vial. Each vial contains 200 mg of tedizolid phosphate and the inactive ingredient, mannitol (105 mg). Sodium hydroxide and hydrochloric acid are used as needed for pH adjustment. When reconstituted as directed with 4 mL of Sterile Water for Injection, each mL contains 50 mg of tedizolid phosphate. The pH of the reconstituted solution is 7.4 to 8.1.

12 CLINICAL PHARMACOLOGY

12.1 Mechanism of Action

Tedizolid is an antibacterial drug [see Microbiology (12.4)].

12.2 Pharmacodynamics

The AUC/minimum inhibitory concentration (MIC) was shown to best correlate with tedizolid activity in animal infection models.

In the mouse thigh infection model of S. aureus, antistaphylococcal killing activity was impacted by the presence of granulocytes. In granulocytopenic mice (neutrophil count <100 cells/mL), bacterial stasis was achieved at a human-equivalent dose of approximately 2000 mg/day; whereas, in non-granulocytopenic animals, stasis was achieved at a human-equivalent dose of approximately 100 mg/day. The safety and efficacy of SIVEXTRO for the treatment of neutropenic patients (neutrophil counts <1000 cells/mm^3) have not been evaluated.

Cardiac Electrophysiology

In a randomized, positive- and placebo-controlled crossover thorough QTc study, 48 enrolled subjects were administered a single oral dose of SIVEXTRO at a therapeutic dose of 200 mg, SIVEXTRO at a supratherapeutic dose of 1200 mg, placebo, and a positive control; no significant effects of SIVEXTRO on heart rate, electrocardiogram morphology, PR, QRS, or QT interval were detected. Therefore, SIVEXTRO does not affect cardiac repolarization.

12.3 Pharmacokinetics

Tedizolid phosphate is a prodrug that is converted by phosphatases to tedizolid, the microbiologically active moiety, following oral and intravenous administration. Only the pharmacokinetic profile of tedizolid is discussed further due to negligible systemic exposure of tedizolid phosphate following oral and intravenous administration. Following multiple once-daily oral or intravenous administration, steady-state concentrations are achieved within approximately three days with tedizolid accumulation of approximately 30% (tedizolid half-life of approximately 12 hours). Pharmacokinetic (PK) parameters of tedizolid following oral and intravenous administration of 200 mg once daily tedizolid phosphate in adults are shown in Table 8.

Table 8: Mean (Standard Deviation) Tedizolid Pharmacokinetic Parameters Following Single and Multiple Oral and Intravenous Administration of 200 mg Once-Daily Tedizolid Phosphate in Adults
Pharmacokinetic Parameters of Tedizolid [Cmax, maximum concentration; Tmax, time to reach Cmax; AUC, area under the concentration-time curve; CL, systemic clearance; CL/F, apparent oral clearance] | Oral |  | Intravenous
Pharmacokinetic Parameters of Tedizolid [Cmax, maximum concentration; Tmax, time to reach Cmax; AUC, area under the concentration-time curve; CL, systemic clearance; CL/F, apparent oral clearance] | Single Dose | Steady State | Single Dose | Steady State
Cmax (mcg/mL) | 2.0 (0.7) | 2.2 (0.6) | 2.3 (0.6) | 3.0 (0.7)
Tmax (hr) [Median (range)] | 2.5 (1.0 - 8.0) | 3.5 (1.0 - 6.0) | 1.1 (0.9 - 1.5) | 1.2 (0.9 - 1.5)
AUC (mcg∙hr/mL) [AUC is AUC0-∞ (AUC from time 0 to infinity) for single-dose administration and AUC0-24 (AUC from time 0 to 24 hours) for multiple-dose administration] | 23.8 (6.8) | 25.6 (8.5) | 26.6 (5.2) | 29.2 (6.2)
CL or CL/F (L/hr) | 7.5 (2.3) | 6.9 (1.7) | 6.4 (1.2) | 5.9 (1.4)

Absorption

Peak plasma tedizolid concentrations are achieved within approximately 3 hours following oral administration of the oral tablet under fasting conditions or at the end of the 1 hour intravenous infusion of tedizolid phosphate. The absolute bioavailability of the oral tablet is approximately 91% and no dosage adjustment is necessary between intravenous and oral administration.

Tedizolid phosphate (oral tablet) may be administered with or without food as total systemic exposure (AUC0-∞) is unchanged between fasted and fed (high-fat, high-calorie) conditions.

Distribution

Protein binding of tedizolid to human plasma proteins is approximately 70 to 90%. The mean steady state volume of distribution of tedizolid in healthy adults following a single intravenous dose of tedizolid phosphate 200 mg ranged from 67 to 80 L (approximately twice total body water). Tedizolid penetrates into the interstitial space fluid of adipose and skeletal muscle tissue with exposure similar to free drug exposure in plasma.

Elimination

Metabolism

Other than tedizolid, which accounts for approximately 95% of the total radiocarbon AUC in plasma, there are no other significant circulating metabolites in humans.

There was no degradation of tedizolid in human liver microsomes indicating tedizolid is unlikely to be a substrate for hepatic CYP450 enzymes.

In vitro studies showed that conjugation of tedizolid is mediated via multiple sulfotransferase (SULT) isoforms (SULT1A1, SULT1A2, and SULT2A1).

Excretion

Following single oral administration of 14C-labeled tedizolid phosphate under fasted conditions in adult healthy volunteers, the majority of elimination occurred via the liver, with 82% of the radioactive dose recovered in feces and 18% in urine, primarily as a non-circulating and microbiologically inactive sulfate conjugate. Most of the elimination of tedizolid (>85%) occurs within 96 hours. Less than 3% of the tedizolid phosphate-administered dose is excreted in feces and urine as unchanged tedizolid.

Specific Populations

Based on the population pharmacokinetic analysis, there are no clinically relevant demographic or clinical patient factors (including age, gender, race, ethnicity, weight, body mass index, and measures of renal or liver function) that impact the pharmacokinetics of tedizolid.

Patients with Hepatic Impairment

Following administration of a single 200 mg oral dose of SIVEXTRO, no clinically meaningful changes in mean tedizolid Cmax and AUC0-∞ were observed in adult patients with moderate (n=8) or severe (n=8) hepatic impairment (Child-Pugh Class B and C) compared to 8 matched healthy control subjects. No dose adjustment is necessary for patients with hepatic impairment.

Patients with Renal Impairment

Following administration of a single 200 mg intravenous dose of SIVEXTRO to 8 adult subjects with severe renal impairment defined as eGFR <30 mL/min/1.73 m^2, the Cmax was essentially unchanged and AUC0-∞ was decreased by less than 10% compared to 8 matched healthy control adult subjects. Hemodialysis does not result in meaningful removal of tedizolid from systemic circulation, as assessed in subjects with end-stage renal disease (eGFR <15 mL/min/1.73 m^2). No dosage adjustment is necessary in patients with renal impairment or patients on hemodialysis.

Geriatric Patients

The pharmacokinetics of tedizolid were evaluated in a Phase 1 study conducted in elderly healthy volunteers (age 65 years and older, with at least 5 subjects at least 75 years old; n=14) compared to younger control subjects (25 to 45 years old; n=14) following administration of a single oral dose of SIVEXTRO 200 mg. There were no clinically meaningful differences in tedizolid Cmax and AUC0-∞ between elderly subjects and younger control subjects. No dosage adjustment of SIVEXTRO is necessary in elderly patients.

Male and Female Patients

The impact of gender on the pharmacokinetics of SIVEXTRO was evaluated in clinical trials of adult healthy males and females and in a population pharmacokinetics analysis. The pharmacokinetics of tedizolid were similar in males and females. No dosage adjustment of SIVEXTRO is necessary based on gender.

Pediatric Patients

The pharmacokinetics of tedizolid was evaluated in clinical studies in pediatric patients from birth (includes neonates who are at least 26 weeks gestational age and weighing at least 1 kg) to less than 18 years of age (N=249).

Compared to adult patients, tedizolid exposures are higher in pediatric patients (12 to <18 years of age, mean weight: 59.7 kg, weight range: 28 kg to 126 kg in Pediatric Trial 1) following multiple dose administration of a once daily dose of 200 mg IV or oral SIVEXTRO (geometric mean Cmax 3.1 vs. 2.0 mcg/mL, AUC24h 28.6 vs. 21.0 mcg*h/mL); however, this increase in exposure is not considered clinically significant.

The predicted steady state mean pharmacokinetic parameters of tedizolid by the pediatric weight-based dosage in Table 2 and Table 3 are shown in Table 9.

Table 9: Geometric Mean (% CV) Predicted Steady-State Exposures Following Multiple Dose Administration of IV or Oral Tedizolid Phosphate Based Upon the Weight-Banded Dosage in Pediatric Patients Birth [Pediatric patients from birth (includes neonates at least 26 weeks gestational age).] to Less than 18 Years
Weight (kg) | Dosage Regimen | Total Daily Dose | Route | Steady-State AUC24h (mcg·h/mL) [AUC0-24 = 2 X AUC0-12 for twice daily dosing.] | Steady-State Cmax (mcg/mL)
1 to less than 2 | 3 mg/kg Twice daily | 6 mg to less than12 mg | IV | 33.1 (29.8) | 2.3 (17.2)
2 to less than 3 | 6 mg Twice daily | 12 mg | IV | 20.8 (25.6) | 1.8 (15.9)
3 to less than 6 | 12 mg Twice daily | 24 mg | IV | 26.4 (34.4) | 2.4 (20.7)
6 to less than 10 | 20 mg Twice daily | 40 mg | IV | 22.5 (43.9) | 2.2 (20.4)
10 to less than 14 | 30 mg Twice daily | 60 mg | IV | 27.6 (32.1) | 2.7 (19.6)
14 to less than 20 | 40 mg Twice daily | 80 mg | IV | 28.4 (22.1) | 2.7 (13.0)
20 to less than 35 | 60 mg Twice daily | 120 mg | IV | 31.4 (29.9) | 2.6 (21.6)
At least 35 | 200 mg Once daily | 200 mg | IV | 30.6 (29.7) | 3.8 (23.9)
At least 35 | 200 mg Once daily | 200 mg | Oral (tablet) | 29.3 (29.7) | 2.5 (24.4)
AUC, area under the concentration-time curve; Cmax, maximum concentration; %CV, coefficient of variation.

Drug Interaction Studies

Drug Metabolizing Enzymes

Transformation via Phase 1 hepatic oxidative metabolism is not a significant pathway for elimination of SIVEXTRO.

Neither SIVEXTRO nor tedizolid detectably inhibited or induced the metabolism of selected CYP enzyme substrates, suggesting that drug-drug interactions based on oxidative metabolism are unlikely.

Membrane Transporters

The potential for tedizolid or tedizolid phosphate to inhibit transport of probe substrates of important drug uptake (OAT1, OAT3, OATP1B1, OATP1B3, OCT1, and OCT2) and efflux transporters (P-gp and BCRP) was tested in vitro. No clinically relevant interactions are expected to occur with these transporters except BCRP.

Coadministration of multiple oral doses of SIVEXTRO (200 mg once daily) increased the Cmax and AUC of rosuvastatin (10 mg single oral dose), a known BCRP substrate, by approximately 55% and 70%, respectively, in healthy adult subjects [see Drug Interactions (7)].

Monoamine Oxidase Inhibition

Tedizolid is a reversible inhibitor of monoamine oxidase (MAO) in vitro. The interaction with MAO inhibitors could not be evaluated in Phase 2 and 3 trials, as subjects taking such medications were excluded from the trials.

Adrenergic Agents

Two placebo-controlled crossover studies were conducted to assess the potential of 200 mg oral SIVEXTRO at steady state to enhance pressor responses to pseudoephedrine and tyramine in healthy adults. No meaningful changes in blood pressure or heart rate were seen with pseudoephedrine. The median tyramine dose required to cause an increase in systolic blood pressure of ≥30 mmHg from pre-dose baseline was 325 mg with SIVEXTRO compared to 425 mg with placebo. Palpitations were reported in 21/29 (72.4%) adult subjects exposed to SIVEXTRO compared to 13/28 (46.4%) exposed to placebo in the tyramine challenge study.

Serotonergic Agents

Serotonergic effects at doses of tedizolid phosphate up to 30-fold above the human equivalent dose did not differ from vehicle control in a mouse model that predicts serotonergic activity. In Phase 3 trials, subjects taking serotonergic agents including antidepressants such as selective serotonin reuptake inhibitors (SSRIs), tricyclic antidepressants, and serotonin 5-hydroxytryptamine (5-HT1) receptor agonists (triptans), meperidine, or buspirone were excluded.

12.4 Microbiology

Mechanism of Action

The antibacterial activity of tedizolid is mediated by binding to the 50S subunit of the bacterial ribosome resulting in inhibition of protein synthesis. Tedizolid inhibits bacterial protein synthesis through a mechanism of action different from that of other non-oxazolidinone class antibacterial drugs; therefore, cross-resistance between tedizolid and other classes of antibacterial drugs is unlikely. The results of in vitro time-kill studies show that tedizolid is bacteriostatic against enterococci, staphylococci, and streptococci.

Resistance

Organisms resistant to oxazolidinones via mutations in chromosomal genes encoding 23S rRNA or ribosomal proteins (L3 and L4) are generally cross-resistant to tedizolid. In the limited number of Staphylococcus aureus strains tested, the presence of the chloramphenicol-florfenicol resistance (cfr) gene did not result in resistance to tedizolid in the absence of chromosomal mutations. Mutations in 23SrRNA (G2576T mutation) have been associated with tedizolid resistance in S. aureus isolates.

Spontaneous mutations conferring reduced susceptibility to tedizolid occur in vitro at a frequency rate of approximately 10^-10.

Interaction with Other Antimicrobial Drugs

In vitro drug combination studies with tedizolid and aztreonam, ceftriaxone, ceftazidime, imipenem, rifampin, trimethoprim/sulfamethoxazole, minocycline, clindamycin, ciprofloxacin, daptomycin, vancomycin, gentamicin, amphotericin B, ketoconazole, and terbinafine demonstrate neither synergy nor antagonism.

Antimicrobial Activity

Tedizolid has been shown to be active against most isolates of the following bacteria, both in vitro and in clinical infections, as described in Indications and Usage (1).

Aerobic bacteria

Gram-positive bacteria

Staphylococcus aureus (including methicillin-resistant [MRSA] and methicillin-susceptible [MSSA] isolates)
Streptococcus pyogenes
Streptococcus agalactiae
Streptococcus anginosus Group (including S. anginosus, S. intermedius, and S. constellatus)
Enterococcus faecalis

The following in vitro data are available, but their clinical significance is unknown. At least 90% of the following bacteria exhibit an in vitro minimum inhibitory concentration (MIC) less than or equal to the susceptible breakpoint for tedizolid against isolates of similar genus or organism group. However, the efficacy of SIVEXTRO in treating clinical infections caused by these bacteria has not been established in adequate and well-controlled clinical trials.

Aerobic bacteria

Gram-positive bacteria

Staphylococcus epidermidis (including methicillin-susceptible and methicillin-resistant isolates)
Staphylococcus haemolyticus
Staphylococcus lugdunensis
Enterococcus faecium

Susceptibility Testing

For specific information regarding susceptibility test interpretive criteria and associated test methods and quality control standards recognized by FDA for this drug, please see: https://www.fda.gov/STIC

13 NONCLINICAL TOXICOLOGY

13.1 Carcinogenesis, Mutagenesis, Impairment of Fertility

Carcinogenicity

Long-term carcinogenicity studies have not been conducted with tedizolid phosphate.

Mutagenesis

Tedizolid phosphate was negative for genotoxicity in all in vitro assays (bacterial reverse mutation (Ames), Chinese hamster lung (CHL) cell chromosomal aberration) and in all in vivo tests (mouse bone marrow micronucleus, rat liver unscheduled DNA synthesis). Tedizolid, generated from tedizolid phosphate after metabolic activation (in vitro and in vivo), was also tested for genotoxicity. Tedizolid was positive in an in vitro CHL cell chromosomal aberration assay, but negative for genotoxicity in other in vitro assays (Ames, mouse lymphoma mutagenicity) and in vivo in a mouse bone marrow micronucleus assay.

Impairment of Fertility

In a fertility study, oral tedizolid phosphate administered in doses of 5, 15, and 50 mg/kg/day for 28 days before mating and during mating to male rats had no adverse effects on the fertility or reproductive performance, including spermatogenesis, at the maximum tested dose (50 mg/kg/day) with a plasma tedizolid AUC approximately 5-fold greater than the plasma AUC value in humans at the maximum recommended human dose (MRHD). Tedizolid phosphate administered in doses of 2.5, 5, and 15 mg/kg/day for 14 days before mating, during mating, and until Gestation Day (GD)7 to female rats also had no adverse effects on the fertility or reproductive performance at doses up to the maximum tested dose of 15 mg/kg/day (approximately 4-fold higher than exposures in humans at the MRHD based on plasma AUC comparison).

13.2 Animal Toxicology and/or Pharmacology

Repeated-oral and intravenous dosing of tedizolid phosphate in rats in 1 month and 3 month toxicology studies produced dose- and time-dependent bone marrow hypocellularity (myeloid, erythroid, and megakaryocyte), with associated reduction in circulating RBCs, WBCs, and platelets. These effects showed evidence of reversibility and occurred at plasma tedizolid exposure levels (AUC) ≥6-fold greater than the plasma exposure associated with the human therapeutic dose. In a 1-month immunotoxicology study in rats, repeated oral dosing of tedizolid phosphate was shown to significantly reduce splenic B cells and T cells and reduce plasma IgG titers. These effects occurred at plasma tedizolid exposure levels (AUC) ≥3-fold greater than the expected human plasma exposure associated with the therapeutic dose.

14 CLINICAL STUDIES

14.1 Acute Bacterial Skin and Skin Structure Infections

Adults

A total of 1333 adults with acute bacterial skin and skin structure infections (ABSSSI) were randomized in two multicenter, multinational, double-blind, non-inferiority trials. Both trials compared SIVEXTRO 200 mg once daily for 6 days versus linezolid 600 mg every 12 hours for 10 days. In Trial 1, patients were treated with oral therapy, while in Trial 2, patients could receive oral therapy after a minimum of one day of intravenous therapy. Patients with cellulitis/erysipelas, major cutaneous abscess, or wound infection were enrolled in the trials. Patients with wound infections could have received aztreonam and/or metronidazole as adjunctive therapy for gram-negative bacterial coverage, if needed. The intent-to-treat (ITT) patient population included all randomized patients.

In Trial 1, 332 patients with ABSSSI were randomized to SIVEXTRO and 335 patients were randomized to linezolid. The majority (91%) of patients treated with SIVEXTRO in Trial 1 were less than 65 years old with a median age of 43 years (range: 18 to 86 years). Patients treated with SIVEXTRO were predominantly male (61%) and White (84%); 13% had BMI ≥35 kg/m^2, 8% had diabetes mellitus, 35% were current or recent intravenous drug users, and 2% had moderate to severe renal impairment. The overall median surface area of infection was 188 cm^2. The types of ABSSSI included were cellulitis/erysipelas (41%), wound infection (29%), and major cutaneous abscess (30%). In addition to local signs and symptoms of infection, patients were also required to have at least one regional or systemic sign of infection at baseline, defined as lymphadenopathy (87% of patients), temperature 38°C or higher (16% of patients), white blood cell count greater than 10,000 cells/mm^3 or less than 4000 cells/mm^3 (42%), or 10% or more band forms on white blood cell differential (4%).

The primary endpoint in Trial 1 was early clinical response defined as no increase from baseline lesion area at 48-72 hours after the first dose and oral temperature of ≤37.6°C, confirmed by a second temperature measurement within 24 hours in the ITT population.

In Trial 2, 332 patients with ABSSSI were randomized to SIVEXTRO and 334 patients were randomized to linezolid. The majority (87%) of patients treated with SIVEXTRO in Trial 2 were less than 65 years old with a median age of 46 years (range: 17 to 86 years). Patients treated with SIVEXTRO were predominantly male (68%) and White (86%); 16% had BMI ≥35 kg/m^2, 10% had diabetes mellitus, 20% were current or recent intravenous drug users, and 4% had moderate to severe renal impairment. The overall median surface area of infection was 231 cm^2. The types of ABSSSI included were cellulitis/erysipelas (50%), wound infection (30%), and major cutaneous abscess (20%). In addition to local signs and symptoms of infection, patients were also required to have at least one regional or systemic sign of infection at baseline, defined as lymphadenopathy (71% of patients), temperature 38°C or higher (31% of patients), white blood cell count greater than 10,000 cells/mm^3 or less than 4000 cells/mm^3 (53%), or 10% or more band forms on white blood cell differential (16%).

The primary endpoint in Trial 2 was early clinical response defined as at least a 20% decrease from baseline lesion area at 48-72 hours after the first dose in the ITT population (Table 10).

Table 10: Early Clinical Response in the ITT Adult Patient Population
 | SIVEXTRO (200 mg) | Linezolid (1200 mg) | Treatment Difference (2-sided 95% CI)
No increase in lesion surface area from baseline and oral temperature of ≤37.6°C, confirmed by a second temperature measurement within 24 hours at 48-72 hours [Primary endpoint for Trial 1; sensitivity analysis for Trial 2]
Trial 1, N | 332 | 335
Responder, n (%) | 264 (79.5) | 266 (79.4) | 0.1 (-6.1, 6.2)
Trial 2, N | 332 | 334
Responder, n (%) | 286 (86.1) | 281 (84.1) | 2.0 (-3.5, 7.3)
At least a 20% decrease from baseline in lesion area at 48-72 hours [Primary endpoint for Trial 2; sensitivity analysis for Trial 1]
Trial 1, N | 332 | 335
Responder, n (%) | 259 (78.0) | 255 (76.1) | 1.9 (-4.5, 8.3)
Trial 2, N | 332 | 334
Responder, n (%) | 283 (85.2) | 276 (82.6) | 2.6 (-3.0, 8.2)
CI=confidence interval

An investigator assessment of clinical response was made at the post-therapy evaluation (PTE) (7 - 14 days after the end of therapy) in the ITT and CE (Clinically Evaluable) populations. Clinical success was defined as resolution or near resolution of most disease-specific signs and symptoms, absence or near resolution of systemic signs of infection if present at baseline (lymphadenopathy, fever, >10% immature neutrophils, abnormal WBC count), and no new signs, symptoms, or complications attributable to the ABSSSI requiring further treatment of the primary lesion (Table 11).

Table 11: Investigator-Assessed Clinical Response at Post-therapy Evaluation in ITT and CE Adult Patient Populations from Two Phase 3 ABSSSI Trials
 | SIVEXTRO (200 mg) n/N (%) | Linezolid (1200 mg) n/N (%) | Treatment Difference (2-sided 95% CI)
Trial 1
ITT | 284/332 (85.5) | 288/335 (86.0) | -0.5 (-5.8, 4.9)
CE | 264/279 (94.6) | 267/280 (95.4) | -0.8 (-4.6, 3.0)
Trial 2
ITT | 292/332 (88.0) | 293/334 (87.7) | 0.3 (-4.8, 5.3)
CE | 268/290 (92.4) | 269/280 (96.1) | -3.7 (-7.7, 0.2)
CI=confidence interval; ITT=intent-to-treat; CE=clinically evaluable

Clinical success by baseline pathogens from the primary infection site or blood cultures for the microbiological intent-to-treat (MITT) patient population for two integrated Phase 3 ABSSSI studies are presented in Table 12 and Table 13.

Table 12: Early Clinical Response by Baseline Pathogen from Two Phase 3 ABSSSI Adult Trials (MITT Population)
Pathogen | No increase in lesion surface area from baseline and oral temperature of ≤37.6°C [Primary endpoint of Trial 1] |  | At least a 20% decrease from baseline in lesion area [Primary endpoint of Trial 2]
Pathogen | SIVEXTRO (200 mg) n/N (%) | Linezolid (1200 mg) n/N (%) | SIVEXTRO (200 mg) n/N (%) | Linezolid (1200 mg) n/N (%)
Staphylococcus aureus | 276/329 (83.9) | 278/342 (81.3) | 280/329 (85.1) | 276/342 (80.7)
Methicillin-resistant S. aureus | 112/141 (79.4) | 113/146 (77.4) | 114/141 (80.9) | 111/146 (76.0)
Methicillin-susceptible S. aureus | 164/188 (87.2) | 167/198 (84.3) | 166/188 (88.3) | 167/198 (84.3)
Streptococcus pyogenes | 27/33 (81.8) | 18/20 (90.0) | 25/33 (75.8) | 16/20 (80.0)
Streptococcus anginosus Group | 22/30 (73.3) | 26/28 (92.9) | 22/30 (73.3) | 25/28 (89.3)
Streptococcus agalactiae | 6/9 (66.7) | 8/10 (80.0) | 6/9 (66.7) | 7/10 (70.0)
Enterococcus faecalis | 7/10 (70.0) | 3/4 (75.0) | 6/10 (60.0) | 1/4 (25.0)
Pooled analysis; n=number of patients in the specific category; N=Number of patients with the specific pathogen isolated from the ABSSSI

Baseline bacteremia in the tedizolid arm with relevant pathogens included two subjects with MRSA, four subjects with MSSA, two subjects with S. pyogenes, one subject with S. agalactiae, and one subject with S. constellatus. All of these subjects were Responders at the 48-72 hour evaluation. At the Post-therapy Evaluation (PTE), 8 of 10 subjects were considered clinical successes.

Table 13: Clinical Response at PTE by Baseline Pathogen from Two Phase 3 ABSSSI Adult Trials (MITT Population)
Pathogen | Clinical Response at PTE
Pathogen | SIVEXTRO (200 mg) n/N (%) | Linezolid (1200 mg) n/N (%)
Staphylococcus aureus | 291/329 (88.5) | 303/342 (88.6)
Methicillin-resistant S. aureus | 118/141 (83.7) | 119/146 (81.5)
Methicillin-susceptible S. aureus | 173/188 (92.0) | 186/198 (93.9)
Streptococcus pyogenes | 30/33 (90.9) | 19/20 (95.0)
Streptococcus anginosus Group | 21/30 (70.0) | 25/28 (89.3)
Streptococcus agalactiae | 8/9 (88.9) | 8/10 (80.0)
Enterococcus faecalis | 7/10 (70.0) | 4/4 (100.0)
Pooled analysis; n=number of patients in the specific category; N=Number of patients with the specific pathogen isolated from the ABSSSI

Baseline bacteremia in the tedizolid arm with relevant pathogens included two subjects with MRSA, four subjects with MSSA, two subjects with S. pyogenes, one subject with S. agalactiae, and one subject with S. constellatus. All of these subjects were Responders at the 48-72 hour evaluation. At the Post-therapy Evaluation (PTE) 8 of 10 subjects were considered clinical successes.

Pediatric Patients

The safety and efficacy of SIVEXTRO were investigated in Pediatric Trials 1 and 2. Pediatric Trial 1 included pediatric patients 12 to < 18 years of age who were investigated in a randomized, single blind, active-controlled trial of 120 patients with clinically documented ABSSSI (91 receiving tedizolid, 29 receiving comparator). Patients were randomized in a 3:1 ratio with stratification by geographic region to receive SIVEXTRO IV and/or oral therapy, dosed 200 mg once daily for 6 days, or comparator IV and/or oral therapy, dosed over 10 days. Comparator therapy was selected by the investigator from a list of 5 IV and 4 oral comparators per local standard of care. The most frequently used comparators were cefazolin (11 patients) and vancomycin (8 patients).

Additionally, Pediatric Trial 2 (NCT03176134) evaluated the safety and efficacy of SIVEXTRO in pediatric patients 4 months to <12 years of age in a randomized, single blind, active-controlled trial of 100 patients with clinically documented ABSSSI (75 receiving tedizolid, 25 receiving comparator). Patients were randomized in a 3:1 ratio to receive SIVEXTRO for 6 to 10 days or comparator for 10 to 14 days. SIVEXTRO (IV and/or oral) was dosed as a weight-based dose of 2 to 2.5 mg/kg every 12 hours or as 200 mg given once daily. Patients who received oral therapy received an oral suspension formulation that is not currently approved for use. Comparator therapy was selected from a pre-specified list by the investigator and dosed per local standard of care.

The primary objective of Pediatric Trials 1 and 2 was to evaluate the safety and tolerability of SIVEXTRO. The trials were not powered for comparative inferential efficacy analysis. Clinical response at the test of cure visit (Day 18-25) was assessed by a blinded investigator in the ITT population (all randomized patients). Clinical successes were required to have resolution or near resolution of all related signs and symptoms such that no further antibacterial therapy was needed. Early clinical response, defined as at least a 20% reduction in lesion size at 48-72 hours after start of treatment, was also assessed in the ITT population.

In Pediatric Trial 1, clinical success at test of cure was 96.7% (88/91) in the tedizolid group and 93.1% (27/29) in the comparator group (difference: 3.6%, 95% CI: -6.3, 13.5). Early clinical response at 48-72 hours was 92.3% (84/91) in the tedizolid group and 96.6% (28/29) in the comparator group (difference: -4.2%, 95% CI: -12.9, 4.4).

In Pediatric Trial 2, clinical success at test of cure was 93.3% (70/75) in the tedizolid group and 92.0% (23/25) in the comparator group (difference: 1.3%, 95% CI: -10.7, 13.4). Early clinical response was not adequately assessed in Pediatric Trial 2 because an in-person outpatient visit at this timepoint was not required during the COVID-19 pandemic.

16 HOW SUPPLIED/STORAGE AND HANDLING

16.1 Tablets

SIVEXTRO Tablets are yellow film-coated oval tablets containing 200 mg of tedizolid phosphate; each tablet is debossed with "TZD" on one side and "200" on the other side.

They are supplied as follows:

HDPE bottles of 30 tablets with child-resistant closure (NDC 67919-041-04)

Unit dose blister packs of 6 tablets (NDC 67919-041-05)

16.2 For Injection

SIVEXTRO is supplied as a sterile, white to off-white lyophilized powder for injection in single-dose vials of 200 mg. Each 200 mg vial must be reconstituted with Sterile Water for Injection and subsequently diluted with 0.9% Sodium Chloride Injection, USP or 5% Dextrose Injection, USP.

They are supplied as follows:

Package of ten 200 mg single-dose vials (NDC 67919-040-02)

16.3 Storage and Handling

SIVEXTRO Tablets and SIVEXTRO for Injection should be stored at 20°C to 25°C (68°F to 77°F); excursions permitted to 15°C to 30°C (59°F to 86°F) [see USP Controlled Room Temperature]. Discard any unused portion of the single-dose vials.

17 PATIENT COUNSELING INFORMATION

Advise the patient to read the FDA-approved patient labeling (Patient Information).

Administration with Food

Patients should be informed that SIVEXTRO Tablets may be taken with or without food and without any dietary restrictions [see Dosage and Administration (2.2, 2.3) and Clinical Pharmacology (12.3)].

Antibacterial Resistance

Patients should be counseled that antibacterial drugs including SIVEXTRO should only be used to treat bacterial infections. They do not treat viral infections (e.g., the common cold). When SIVEXTRO is prescribed to treat a bacterial infection, patients should be told that although it is common to feel better early in the course of therapy, the medication should be taken exactly as directed. Skipping doses or not completing the full course of therapy may (1) decrease the effectiveness of the immediate treatment and (2) increase the likelihood that bacteria will develop resistance and will not be treatable by SIVEXTRO or other antibacterial drugs in the future [see Indications and Usage (1.2)].

Missed Doses

Patients should be informed that if they miss a SIVEXTRO oral dose, they should take the dose as soon as possible anytime up to 8 hours prior to their next scheduled dose. If less than 8 hours remains before the next dose, then they should wait until their next scheduled dose. Patients should take the prescribed number of doses [see Dosage and Administration (2.2, 2.3)].

Potentially Serious Adverse Reactions

Patients should be advised that diarrhea is a common problem caused by antibacterial drugs including SIVEXTRO and usually resolves when the drug is discontinued. Sometimes after starting treatment with antibacterial drugs, patients can develop frequent watery and bloody stools (with or without stomach cramps and fever) even as late as two or more months after having taken the last dose of the antibacterial drug and may be a sign of a more serious intestinal infection [see Warnings and Precautions (5.2) and Adverse Reactions (6.1)]. If this occurs, patients should contact their healthcare provider as soon as possible.

Embryo-Fetal Toxicity

Based on animal data, advise pregnant women and females of reproductive potential of the potential risk to a fetus. Advise females to inform their healthcare provider of a known or suspected pregnancy [see Use in Specific Populations (8.1)].

Manuf. for: Merck Sharp & Dohme LLC
Rahway, NJ 07065, USA

Sivextro Tablets
Manufactured by: Patheon Inc.
Whitby, Ontario, L1N 5Z5 Canada

Sivextro for Injection
Manufactured by: Patheon Italia S.p.A.
03013, Ferentino, FR Italy

For patent information: www.msd.com/research/patent

Copyright © 2015-2025 Merck & Co., Inc., Rahway, NJ, USA, and its affiliates.
All rights reserved.

uspi-mk1986-mf-2504r012

Patient Information
SIVEXTRO®(sih-vex-tro)
(tedizolid phosphate)
tablets

What you need to know about SIVEXTRO

- Before you take this medicine, be sure you understand what it is for and how to take it safely.
- Keep this information.
- If you have questions about this medicine, ask your doctor or pharmacist.
- Every time you get a refill, look at the Patient Information sheet that comes with it. There may be new information.
- Remember that your doctor has prescribed this medicine only for you. Never give it to anyone else.

What is SIVEXTRO?

SIVEXTRO tablet is for adults and for children weighing at least 77 pounds (35 kg) who have a skin infection or an infection in the tissue below the skin. SIVEXTRO is an antibiotic that works by stopping the growth of certain bacteria.

What should I tell my doctor before taking SIVEXTRO?

Medical Conditions

Tell your doctor if you:

- have diarrhea or have ever had diarrhea while taking antibiotics. Tell your doctor, even if you had diarrhea that occurred up to 2 months after you took the antibiotic.
- are allergic to tedizolid phosphate or any of the ingredients in SIVEXTRO. See the end of this Patient Information for a complete list of ingredients in SIVEXTRO.
- are pregnant or plan to get pregnant, tell your doctor if you become pregnant while taking SIVEXTRO. It is not known if SIVEXTRO will harm your baby while you are pregnant. You and your doctor should decide together if you will take SIVEXTRO.
- are breastfeeding or plan to breastfeed, tell your doctor before you take SIVEXTRO. It is not known if SIVEXTRO passes into your breast milk. You and your doctor should decide together if you will take SIVEXTRO or breastfeed.

Are you taking other medicines?

- SIVEXTRO can affect the way other medicines work, and other medicines can affect how SIVEXTRO works. Some medicines cannot be taken with SIVEXTRO at all. Your doctor will tell you if it is safe to take SIVEXTRO with other medicines.
- It is especially important to tell your doctor if you take any of the following medicines:
  - Methotrexate (for cancer or rheumatoid arthritis)
  - Topotecan (for cancer)
  - Rosuvastatin (for cholesterol)
- Tell your doctor about all of the medicines you take, including prescription and over-the-counter medicines, vitamins, and herbal and dietary supplements.
- Know the medicines you take. Keep a list of them and show the list to your doctor and pharmacist when you get a new medicine.

How do I take SIVEXTRO?

- Do not give SIVEXTRO tablets to children weighing less than 77 pounds (35 kg).
- Take SIVEXTRO exactly how your doctor tells you to take it.
- Take 1 SIVEXTRO tablet 1 time each day.
- Take SIVEXTRO for 6 days, at the same time every day.
- Take SIVEXTRO by mouth, with or without food.

What if I forget to take SIVEXTRO?

- If you miss a dose, take the missed dose as soon as you remember.
  If it is less than 8 hours until your next dose, skip the missed dose and take the next tablet at the time you usually take it.
- Do not take 2 doses of SIVEXTRO at the same time to make up for a missed dose.
- If you are not sure how to take SIVEXTRO, call your doctor or pharmacist.
- Take all 6 tablets to finish your SIVEXTRO, even if you have missed a dose.

If you do not finish your medicine, SIVEXTRO may not work.

You may get sick again and the remaining bacteria may be harder to treat.

What are the possible side effects of SIVEXTRO?

SIVEXTRO may cause serious side effects, including diarrhea from C-diff (Clostridioides difficile) infection. Call your healthcare provider right away if you get stomach cramps, fever, watery diarrhea, diarrhea that does not go away, or bloody stools. C-diff infection can happen 2 or more months after you have finished your antibacterial medicine.

C-diff is an infection of your intestines (bowels) that can happen with many antibiotics like SIVEXTRO and may cause mild diarrhea to life-threatening swelling of your intestines (colitis).

Common side effects of SIVEXTRO include:

- nausea
- headache
- dizziness
- vomiting

- diarrhea
- increased liver enzymes
- painful swelling or inflammation of veins (phlebitis)

Some less common side effects are:

Problems with your skin

- itching, red or itchy rash, hives, acne
- hot flushes or feeling like you are blushing or your face, neck or chest is red
- not able to feel something as well
- a tingling or prickling sensation

Problems with your sleep

- hard time sleeping

Problems with your body

- numbness
- facial paralysis

Problems with infections

- vagina that is infected, inflamed, or itchy
- fungal infections of skin, mouth

Problems with your eyes

- eye strain
- blurred or impaired vision
- seeing dots or spots in your eyes

Problems with your heart

- Your heartbeat does not feel normal. It could feel like your heart is beating too fast or pumping harder than usual.

Problems with your vascular system

- high blood pressure

Problems with your blood work

Your doctor may tell you that you have the following while taking SIVEXTRO:

- a low white blood cell count
- anemia (low red blood cells)
- low platelet count, the small cells involved in clotting your blood

Side effects where the frequency is not known:

- bleeding or bruising easily

If you have any side effect that bothers you or does not go away, tell your doctor.

These are not all the possible side effects of SIVEXTRO. For information, ask your doctor or pharmacist. Call your doctor for medical advice about side effects. You may report side effects to FDA at 1-800-FDA-1088.

How should I store SIVEXTRO?

- Store SIVEXTRO at room temperature between 68°F to 77°F (20°C to 25°C).
- Keep SIVEXTRO and all medicines out of the reach of children.

General information about SIVEXTRO.

- Medicines are sometimes prescribed for purposes that are not mentioned here.
- Do not use SIVEXTRO for a condition for which it was not prescribed.

What if I have questions?

- Call your doctor.
- Call the company that makes SIVEXTRO at 1-800-444-2080.
- Go to the website – www.SIVEXTRO.com.
- You can ask your doctor or pharmacist for information about SIVEXTRO that is written for health professionals.

What are the ingredients in SIVEXTRO?

- The active ingredient: tedizolid phosphate.
- The inactive ingredients: crospovidone, magnesium stearate, mannitol, microcrystalline cellulose, and povidone. Film coating: polyethylene glycol/macrogol, polyvinyl alcohol, talc, titanium dioxide, and yellow iron oxide.

Manuf. for: Merck Sharp & Dohme LLC
Rahway, NJ 07065, USA

Sivextro tablets Manufactured by: Patheon Inc., Whitby, Ontario, L1N 5Z5 Canada

Sivextro for injection Manufactured by: Patheon Italia S.p.A., 03013, Ferentino, FR Italy

For patent information: www.msd.com/research/patent. The trademarks depicted herein are owned by their respective companies.

Copyright © 2017-2025 Merck & Co., Inc., Rahway, NJ, USA, and its affiliates. All rights reserved.

usppi-mk1986-mf-2504r005

This Patient Information has been approved by the U.S. Food and Drug Administration Revised: 4/2025

PRINCIPAL DISPLAY PANEL - 200 mg Tablet Bottle Label

NDC 67919-041-04
30 tablets

Sivextro®
(tedizolid phosphate) tablets

200 mg per tablet

Rx only

PRINCIPAL DISPLAY PANEL - 200 mg Tablet Blister Pack Carton

NDC 67919-041-05
6 tablets

Sivextro®
(tedizolid phosphate) tablets

200 mg per tablet

Rx only

PRINCIPAL DISPLAY PANEL - 200 mg Vial Carton

NDC 67919-040-02
10 single-dose vials

Sivextro®
(tedizolid phosphate) for injection

200 mg per vial
For Intravenous Infusion

Must be reconstituted and further
diluted prior to administration
by intravenous infusion.

Sterile
Rx only